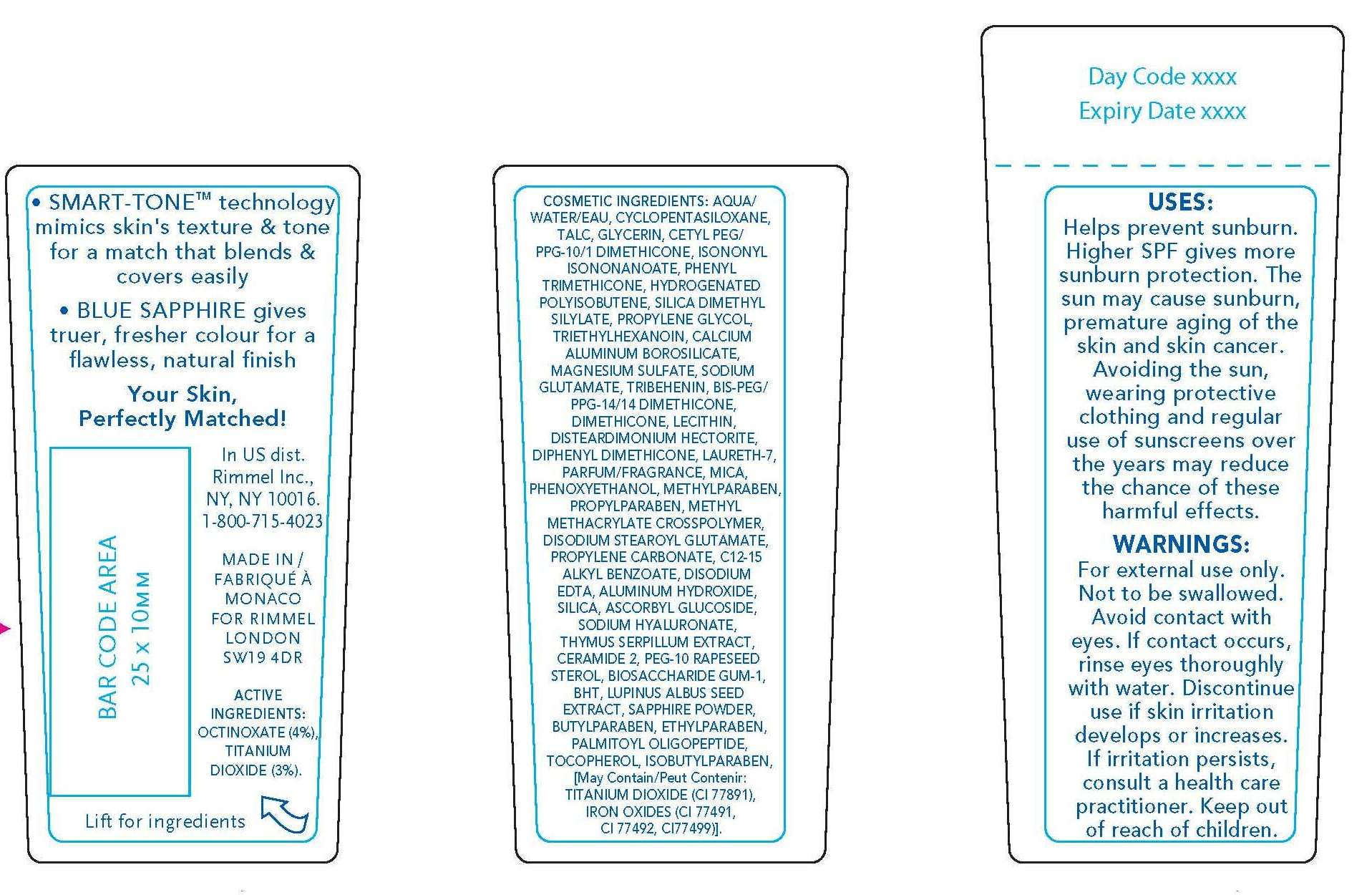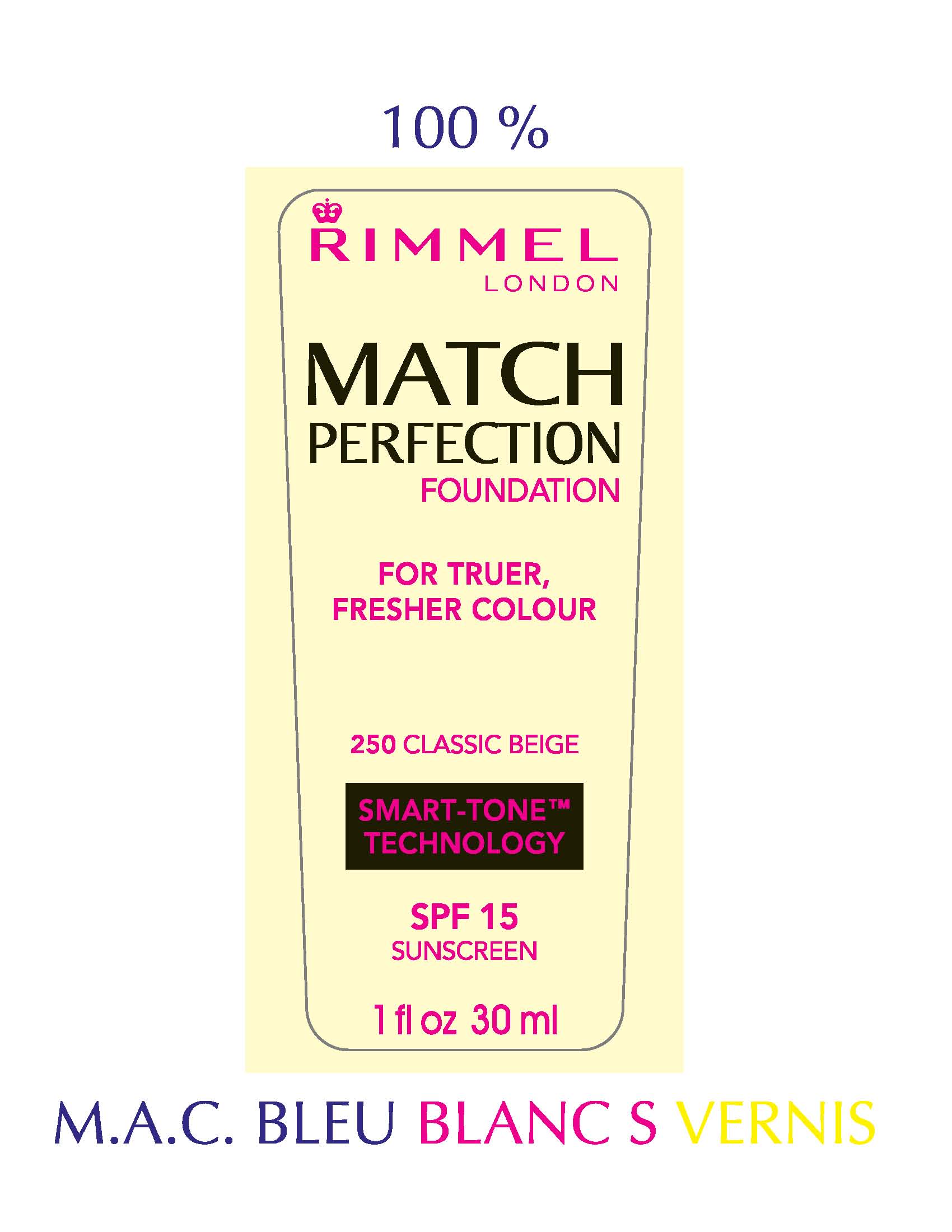 DRUG LABEL: Rimmel London
NDC: 59351-0320 | Form: LIQUID
Manufacturer: Lancaster S.A.M.
Category: otc | Type: HUMAN OTC DRUG LABEL
Date: 20101006

ACTIVE INGREDIENTS: OCTINOXATE 1.2 mL/30 mL; TITANIUM DIOXIDE 0.9 mL/30 mL
INACTIVE INGREDIENTS: WATER; CYCLOMETHICONE 5; TALC; GLYCERIN; DIMETHICONE; ISONONYL ISONONANOATE; PHENYL TRIMETHICONE; SILICON DIOXIDE; PROPYLENE GLYCOL; TRIETHYLHEXANOIN; MAGNESIUM SULFATE, UNSPECIFIED; MONOSODIUM GLUTAMATE; TRIBEHENIN; EGG PHOSPHOLIPIDS; HECTORITE; LAURETH-7; MICA; PHENOXYETHANOL; METHYLPARABEN; PROPYLPARABEN; METHYL METHACRYLATE; PROPYLENE CARBONATE; ALKYL (C12-15) BENZOATE; EDETATE DISODIUM; ALUMINUM HYDROXIDE; SILICON DIOXIDE; HYALURONATE SODIUM; THYMUS; BIOSACCHARIDE GUM-1; BUTYLATED HYDROXYTOLUENE; BUTYLPARABEN; ETHYLPARABEN; ALPHA-TOCOPHEROL; ISOBUTYLPARABEN; TITANIUM DIOXIDE; IRON

Rimmel London Match Perfection Foundation Classic Beige (250) SPF 15 Sunscreen

DESCRIPTION

SMART-TONE technology
mimics skin's texture and tone
for a match that blends and
covers easily
BLUE SAPPHIRE gives
truer, fresher colour for a
flawless, natural finish
Your Skin,
Perfectly Matched!

ACTIVE
INGREDIENTS:
OCTINOXATE (4%),
TITANIUM
DIOXIDE (3%).

INACTIVE INGREDIENT

COSMETIC INGREDIENTS: AQUA/
WATER/EAU, CYCLOPENTASILOXANE,
TALC, GLYCERIN, CETYL PEG/
PPG-10/1 DIMETHICONE, ISONONYL
ISONONANOATE, PHENYL
TRIMETHICONE, HYDROGENATED
POLYISOBUTENE, SILICA DIMETHYL
SILYLATE, PROPYLENE GLYCOL,
TRIETHYLHEXANOIN, CALCIUM
ALUMINUM BOROSILICATE,
MAGNESIUM SULFATE, SODIUM
GLUTAMATE, TRIBEHENIN, BIS-PEG/
PPG-14/14 DIMETHICONE,
DIMETHICONE, LECITHIN,
DISTEARDIMONIUM HECTORITE,
DIPHENYL DIMETHICONE, LAURETH-7,
PARFUM/FRAGRANCE, MICA,
PHENOXYETHANOL, METHYLPARABEN,
PROPYLPARABEN, METHYL
METHACRYLATE CROSSPOLYMER,
DISODIUM STEAROYL GLUTAMATE,
PROPYLENE CARBONATE, C12-15
ALKYL BENZOATE, DISODIUM
EDTA, ALUMINUM HYDROXIDE,
SILICA, ASCORBYL GLUCOSIDE,
SODIUM HYALURONATE,
THYMUS SERPILLUM EXTRACT,
CERAMIDE 2, PEG-10 RAPESEED
STEROL, BIOSACCHARIDE GUM-1,
BHT, LUPINUS ALBUS SEED
EXTRACT, SAPPHIRE POWDER,
BUTYLPARABEN, ETHYLPARABEN,
PALMITOYL OLIGOPEPTIDE,
TOCOPHEROL, ISOBUTYLPARABEN,
[May Contain/Peut Contenir:
TITANIUM DIOXIDE (CI 77891),
IRON OXIDES (CI 77491,
CI 77492, CI77499)].

USES:
Helps prevent sunburn.
Higher SPF gives more
sunburn protection. The
sun may cause sunburn,
premature aging of the
skin and skin cancer.
Avoiding the sun,
wearing protective
clothing and regular
use of sunscreens over
the years may reduce
the chance of these
harmful effects.

WARNINGS:
For external use only.
Not to be swallowed.
Avoid contact with
eyes. If contact occurs,
rinse eyes thoroughly
with water. Discontinue
use if skin irritation
develops or increases.
If irritation persists,
consult a health care
practitioner. Keep out
of reach of children.

PACKAGE LABEL

RIMMEL LONDON
MATCH PERFECTION FOUNDATION
FOR TRUER, FRESHER COLOUR
SMART-TONE TECHNOLOGY
SPF 15 SUNSCREEN
1 fl oz 30 ml